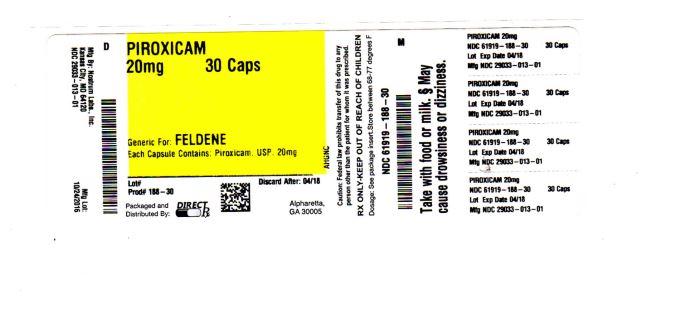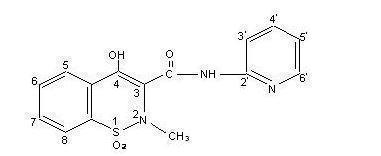 DRUG LABEL: piroxicam
NDC: 61919-188 | Form: CAPSULE
Manufacturer: DIRECT RX
Category: prescription | Type: HUMAN PRESCRIPTION DRUG LABEL
Date: 20200121

ACTIVE INGREDIENTS: PIROXICAM 20 mg/1 1

piroxicam

BOXED WARNING SECTION

Cardiovascular Risk

- NSAIDs may cause an increased risk of serious cardiovascular thrombotic events, myocardial infarction, and stroke, which can be fatal. This risk may increase with duration of use. Patient's with cardiovascular disease or risk factors for cardiovascular disease may be at greater risk (see WARNINGS).
- Piroxicam Capsules USP is contraindicated for the treatment of peri-operative pain in the setting of coronary artery bypass graft (CABG) surgery (see WARNINGS).

Gastrointestinal Risk

- NSAID's cause an increased risk of serious gastrointestinal adverse events including bleeding, ulceration, and perforation of the stomach or intestines, which can be fatal. These events can occur at any time during use and without warning symptoms. Elderly patients are at greater risk for serious gastrointestinal events (see WARNINGS).

DESCRIPTION SECTION

Piroxicam Capsules USP contains piroxicam which is a member of the oxicam group of nonsteroidal anti-inflammatory drugs (NSAIDs). Each ivory opaque/Swedish orange opaque capsule contains 10 mg piroxicam; each Swedish orange opaque/Swedish orange opaque capsule contains 20 mg piroxicam for oral administration. The chemical name for piroxicam is 4-hydroxyl-2-methyl-N-2-pyridinyl-2H-1,2,-benzothiazine-3-carboxamide 1,1-dioxide. Piroxicam occurs as a white crystalline solid, sparingly soluble in water, dilute acid and most organic solvents. It is slightly soluble in alcohol and in aqueous solutions. It exhibits a weakly acidic 4-hydroxy proton (pKa 5.1) and a weakly basic pyridyl nitrogen (pKa 1.8). The molecular weight of piroxicam is 331.35. Its molecular formula is C15H13N3O4S and it has the following structural formula:

The inactive ingredients in Piroxicam Capsules USP include: hard gelatin capsules (which may contain FD&C Blue1, FD&C Red 40, D&C Yellow 10, titanium dioxide and gelatin inactive ingredients), corn starch, lactose, magnesium stearate and sodium lauryl sulfate.

CLINICAL PHARMACOLOGY SECTION

Pharmacodynamics

Piroxicam Capsules USP is a nonsteroidal anti-inflammatory drug (NSAID) that exhibits anti-inflammatory, analgesic, and antipyretic activities in animal models. The mechanism of action of piroxicam, like that of other NSAIDs, is not completely understood but may be related to prostaglandin synthetase inhibition.

PharmacokineticsAbsorption

Piroxicam is well absorbed following oral administration. Drug plasma concentrations are proportional for 10 and 20 mg doses and generally peak within three to five hours after medication. The prolonged half-life (50 hours) results in the maintenance of relatively stable plasma concentrations throughout the day on once daily doses and to significant accumulation upon multiple dosing. A single 20-mg dose generally produces peak piroxicam plasma levels of 1.5 to 2 mcg/mL, while maximum drug plasma concentrations, after repeated daily ingestion of 20 mg Piroxicam Capsules USP, usually stabilize at 3–8 mcg/mL. Most patients approximate steady state plasma levels within 7–12 days. Higher levels, which approximate steady state at two to three weeks, have been observed in patients in whom longer plasma half-lives of piroxicam occurred.

With food there is a slight delay in the rate but not the extent of absorption following oral administration. The concomitant administration of antacids (aluminum hydroxide or aluminum hydroxide with magnesium hydroxide) have been shown to have no effect on the plasma levels of orally administered piroxicam.

Distribution

The apparent volume of distribution of piroxicam is approximately 0.14 L/kg. Ninety-nine percent of plasma piroxicam is bound to plasma proteins. Piroxicam is excreted into human milk. The presence in breast milk has been determined during initial and long-term conditions (52 days). Piroxicam appeared in breast milk at about 1% to 3% of the maternal concentration. No accumulation of piroxicam occurred in milk relative to that in plasma during treatment.

Metabolism

Metabolism of piroxicam occurs by hydroxylation at the 5 position of the pyridyl side chain and conjugation of this product; by cyclodehydration; and by a sequence of reactions involving hydrolysis of the amide linkage, decarboxylation, ring contraction and N-demethylation. In vitro studies indicate cytochrome P4502C9 (CYP2C9) as the main enzyme involved in the formation to the 5'-hydroxy-piroxicam, the major metabolite (see Pharmacogenetics, and Special Populations, Poor Metabolizers of CYP2C9 Substrates). The biotransformation products of piroxicam metabolism are reported to not have any anti-inflammatory activity.

Higher systemic exposure of piroxicam has been noted in subjects with CYP2C9 polymorphisms compared to normal metabolizer type subjects (see Pharmacogenetics, and Special Populations, Poor Metabolizers of CYP2C9 Substrates).

Excretion

Piroxicam and its biotransformation products are excreted in urine and feces, with about twice as much appearing in the urine as in the feces. Approximately 5% of a piroxicam dose is excreted unchanged. The plasma half-life (T½) for piroxicam is approximately 50 hours.

Pharmacogenetics

CYP2C9 activity is reduced in individuals with genetic polymorphisms, such as the CYP2C9*2 and CYP2C9*3 polymorphisms. Limited data from one published report that included nine subjects each with heterozygous CYP2C9*1/*2 and CYP2C9*1/*3 genotypes and one subject with the homozygous CYP2C9*3/*3 genotype showed piroxicam systemic levels that were 1.7-, 1.7- and 5.3-fold, respectively, higher compared to the 17 subjects with CYP2C9*1/*1 or normal metabolizer genotype. The pharmacokinetics of piroxicam have not been evaluated in subjects with other CYP2C9 polymorphisms, such as *5, *6, *9 and *11. It is estimated that the frequency of the homozygous *3/*3 genotype is 0.3% to 1.0% in various ethnic groups.

Special PopulationsPediatric

Piroxicam Capsules USP has not been investigated in pediatric patients.

Race

Pharmacokinetic differences due to race have not been identified.

Hepatic Insufficiency

The effects of hepatic disease on piroxicam pharmacokinetics have not been established. However, a substantial portion of piroxicam elimination occurs by hepatic metabolism. Consequently, patients with hepatic disease may require reduced doses of piroxicam as compared to patients with normal hepatic function.

Poor Metabolizers of CYP2C9 Substrates

Patients who are known or suspected to be poor CYP2C9 metabolizers based on genotype or previous history/experience with other CYP2C9 substrates (such as warfarin and phenytoin) should be administered piroxicam with caution as they may have abnormally high plasma levels due to reduced metabolic clearance.

Renal Insufficiency

Piroxicam pharmacokinetics have been investigated in patients with renal insufficiency. Studies indicate patients with mild to moderate renal impairment may not require dosing adjustments. However, the pharmacokinetic properties of Piroxicam in patients with severe renal insufficiency or those receiving hemodialysis are not known.

Other Information

In controlled clinical trials, the effectiveness of piroxicam has been established for both acute exacerbations and long-term management of rheumatoid arthritis and osteoarthritis.

The therapeutic effects of piroxicam are evident early in the treatment of both diseases with a progressive increase in response over several (8–12) weeks. Efficacy is seen in terms of pain relief and, when present, subsidence of inflammation.

Doses of 20 mg/day piroxicam display a therapeutic effect comparable to therapeutic doses of aspirin, with a lower incidence of minor gastrointestinal effects and tinnitus.

Piroxicam has been administered concomitantly with fixed doses of gold and corticosteroids. The existence of a "steroid-sparing" effect has not been adequately studied to date.

INDICATIONS & USAGE SECTION

Carefully consider the potential benefits and risks of Piroxicam Capsules USP and other treatment options before deciding to use Piroxicam Capsules USP. Use the lowest effective dose for the shortest duration consistent with individual patient treatment goals (see WARNINGS).

Piroxicam Capsules USP is indicated:

- For relief of the signs and symptoms of osteoarthritis.
- For relief of the signs and symptoms of rheumatoid arthritis.

CONTRAINDICATIONS SECTION

CONTRAINDICATIONS

Piroxicam Capsules USP is contraindicated in patients with known hypersensitivity to piroxicam.

Piroxicam Capsules USP should not be given to patients who have experienced asthma, urticaria or allergic-type reactions after taking aspirin or other NSAIDs. Severe, rarely fatal, anaphylactic-like reactions to NSAIDs have been reported in such patients (see WARNINGS: Anaphylactoid Reactions and PRECAUTIONS: Preexisting Asthma).

Piroxicam Capsules USP is contraindicated for the treatment of peri-operative pain in the setting of coronary artery bypass graft (CABG) surgery (see WARNINGS).

WARNINGS SECTION

CARDIOVASCULAR EFFECTSCardiovascular Thrombotic Events

Clinical trials of several COX-2 selective and nonselective NSAIDs of up to three years duration have shown an increased risk of serious cardiovascular (CV) thrombotic events, myocardial infarction, and stroke, which can be fatal. All NSAIDs, both COX-2 selective and nonselective, may have a similar risk. Patients with known CV disease or risk factors for CV disease may be at greater risk. To minimize the potential risk for an adverse CV event in patients treated with an NSAID, the lowest effective dose should be used for the shortest duration possible. Physicians and patients should remain alert for the development of such events, even in the absence of previous CV symptoms. Patients should be informed about the signs and/or symptoms of serious CV events and the steps to take if they occur.

There is no consistent evidence that concurrent use of aspirin mitigates the increased risk of serious CV thrombotic events associated with NSAID use. The concurrent use of aspirin and an NSAID does increase the risk of serious GI events (see GI WARNINGS).

Two large, controlled clinical trials of a COX-2 selective NSAID for the treatment of pain in the first 10–14 days following CABG surgery found an increased incidence of myocardial infarction and stroke (see CONTRAINDICATIONS).

Hypertension

NSAIDs, including Piroxicam Capsules USP, can lead to onset of new hypertension or worsening of pre-existing hypertension, either of which may contribute to the increased incidence of CV events. Patients taking thiazides or loop diuretics may have impaired response to these therapies when taking NSAIDs. NSAIDs, including Piroxicam Capsules USP, should be used with caution in patients with hypertension. Blood pressure (BP) should be monitored closely during the initiation of NSAID treatment and throughout the course of therapy.

Congestive Heart Failure and Edema

Fluid retention and edema have been observed in some patients taking NSAIDs. Piroxicam Capsules USP should be used with caution in patients with fluid retention or heart failure.

Gastrointestinal Effects - Risk of Ulceration, Bleeding and Perforation

NSAIDs, including Piroxicam Capsules USP, can cause serious gastrointestinal (GI) adverse events including inflammation, bleeding, ulceration, and perforation of the stomach, small intestine, or large intestine, which can be fatal. These serious adverse events can occur at any time, with or without warning symptoms, in patients treated with NSAIDs. Only one in five patients, who develop a serious upper GI adverse event on NSAID therapy, is symptomatic. Upper GI ulcers, gross bleeding, or perforation caused by NSAIDs occur in approximately 1% of patients treated for 3–6 months, and in about 2–4% of patients treated for one year. These trends continue with longer duration of use, increasing the likelihood of developing a serious GI event at some time during the course of therapy. However, even short-term therapy is not without risk.

NSAIDs should be prescribed with extreme caution in those with a prior history of ulcer disease or gastrointestinal bleeding. Patients with a prior history of peptic ulcer disease and/or gastrointestinal bleeding who use NSAIDs have a greater than 10-fold increased risk for developing a GI bleed compared to patients with neither of these risk factors. Other factors that increase the risk of GI bleeding in patients treated with NSAIDs include concomitant use of oral corticosteroids or anticoagulants, longer duration of NSAID therapy, smoking, use of alcohol, older age, and poor general health status. Most spontaneous reports of fatal GI events are in elderly or debilitated patients and therefore, special care should be taken in treating this population.

To minimize the potential risk for an adverse GI event in patients treated with an NSAID, the lowest effective dose should be used for the shortest possible duration. Patients and physicians should remain alert for signs and symptoms of GI ulcerations and bleeding during NSAID therapy and promptly initiate additional evaluation and treatment if a serious GI event is suspected. This should include discontinuation of the NSAID until a serious GI adverse event is ruled out. For high-risk patients, alternate therapies that do not involve NSAIDs should be considered.

Renal Effects

Long-term administration of NSAIDs has resulted in renal papillary necrosis and other renal injury. Renal toxicity has also been seen in patients in whom renal prostaglandins have a compensatory role in the maintenance of renal perfusion. In these patients, administration of a nonsteroidal anti-inflammatory drug may cause a dose-dependent reduction in prostaglandin formation and, secondarily, in renal blood flow, which may precipitate overt renal decompensation. Patients at greatest risk of this reaction are those with impaired renal function, heart failure, liver dysfunction, those taking diuretics and ACE inhibitors, and the elderly. Discontinuation of NSAID therapy is usually followed by recovery to the pretreatment state.

Advanced Renal Disease

No information is available from controlled clinical studies regarding the use of Piroxicam Capsules USP in patients with advanced renal disease. Therefore, treatment with Piroxicam Capsules USP is not recommended in these patients with advanced renal disease. If Piroxicam Capsules USP therapy must be initiated, close monitoring of the patient's renal function is advisable.

Anaphylactoid Reactions

As with other NSAIDs, anaphylactoid reactions may occur in patients without known prior exposure to Piroxicam Capsules USP. Piroxicam Capsules USP should not be given to patients with the aspirin triad. This symptom complex typically occurs in asthmatic patients who experience rhinitis with or without nasal polyps, or who exhibit severe, potentially fatal bronchospasm after taking aspirin or other NSAIDs (see CONTRAINDICATIONS and PRECAUTIONS: Preexisting Asthma). Emergency help should be sought in cases where an anaphylactoid reaction occurs.

Skin Reactions

NSAIDs, including Piroxicam Capsules USP, can cause serious skin adverse events such as exfoliative dermatitis, Stevens-Johnson Syndrome (SJS), and toxic epidermal necrolysis (TEN), which can be fatal. These serious events may occur without warning. Patients should be informed about the signs and symptoms of serious skin manifestations and use of the drug should be discontinued at the first appearance of skin rash or any other sign of hypersensitivity.

Other Hypersensitivity Reactions

A combination of dermatological and/or allergic signs and symptoms suggestive of serum sickness have occasionally occurred in conjunction with the use of piroxicam. These include arthralgias, pruritus, fever, fatigue, and rash including vesiculobullous reactions and exfoliative dermatitis.

Pregnancy

In late pregnancy, as with other NSAIDs, Piroxicam Capsules USP should be avoided because it may cause premature closure of the ductus arteriosus.

PRECAUTIONS SECTION

General

Piroxicam Capsules USP cannot be expected to substitute for corticosteroids or to treat corticosteroid insufficiency. Abrupt discontinuation of corticosteroids may lead to disease exacerbation. Patients on prolonged corticosteroid therapy should have their therapy tapered slowly if a decision is made to discontinue corticosteroids.

The pharmacological activity of Piroxicam Capsules USP in reducing fever and inflammation may diminish the utility of these diagnostic signs in detecting complications of presumed noninfectious, painful conditions.

Hepatic Effects

Borderline elevations of one or more liver tests may occur in up to 15% of patients taking NSAIDs including Piroxicam Capsules USP. These laboratory abnormalities may progress, may remain unchanged, or may be transient with continuing therapy. Notable elevations of ALT or AST (approximately three or more times the upper limit of normal) have been reported in approximately 1% of patients in clinical trials with NSAIDs. In addition, rare cases of severe hepatic reactions, including jaundice and fatal fulminant hepatitis, liver necrosis and hepatic failure, some of them with fatal outcomes have been reported.

A patient with symptoms and/or signs suggesting liver dysfunction, or in whom an abnormal liver test has occurred, should be evaluated for evidence of the development of more severe hepatic reaction while on therapy with Piroxicam Capsules USP. If clinical signs and symptoms consistent with liver disease develop, or if systemic manifestations occur (e.g., eosinophilia, rash, etc.), Piroxicam Capsules USP should be discontinued (see ADVERSE REACTIONS).

Hematological Effects

Anemia is sometimes seen in patients receiving NSAIDs, including Piroxicam Capsules USP. This may be due to fluid retention, occult or gross GI blood loss, or an incompletely described effect upon erythropoiesis. Patients on long-term treatment with NSAIDs, including Piroxicam Capsules USP, should have their hemoglobin or hematocrit checked if they exhibit any signs or symptoms of anemia.

NSAIDs inhibit platelet aggregation and have been shown to prolong bleeding time in some patients. Unlike aspirin, their effect on platelet function is quantitatively less, of shorter duration, and reversible. Patients receiving Piroxicam Capsules USP who may be adversely affected by alterations in platelet function, such as those with coagulation disorders or patients receiving anticoagulants, should be carefully monitored.

Ophthalmologic Effects

Because of reports of adverse eye findings with nonsteroidal anti-inflammatory agents, it is recommended that patients who develop visual complaints during treatment with Piroxicam Capsules USP have ophthalmic evaluations.

Preexisting Asthma

Patients with asthma may have aspirin-sensitive asthma. The use of aspirin in patients with aspirin-sensitive asthma has been associated with severe bronchospasm which can be fatal. Since crossreactivity, including bronchospasm, between aspirin and other nonsteroidal anti-inflammatory drugs has been reported in such aspirin-sensitive patients, Piroxicam Capsules USP should not be administered to patients with this form of aspirin sensitivity and should be used with caution in patients with preexisting asthma.

Information for Patients

Patients should be informed of the following information before initiating therapy with an NSAID and periodically during the course of ongoing therapy. Patients should also be encouraged to read the NSAID Medication Guide that accompanies each prescription dispensed.

- Piroxicam Capsules USP, like other NSAIDs, may cause CV side effects, such as MI or stroke, which may result in hospitalization and even death. Although serious CV events can occur without warning symptoms, patients should be alert for the signs and symptoms of chest pain, shortness of breath, weakness, slurring of speech, and should ask for medical advice when observing any indicative sign or symptoms. Patients should be apprised of the importance of this follow-up (see WARNINGS, Cardiovascular Effects).
- Piroxicam Capsules USP, like other NSAIDs, can cause GI discomfort and, rarely, serious GI side effects, such as ulcers and bleeding, which may result in hospitalization and even death. Although serious GI tract ulcerations and bleeding can occur without warning symptoms, patients should be alert for the signs and symptoms of ulcerations and bleeding, and should ask for medical advice when observing any indicative sign or symptoms including epigastric pain, dyspepsia, melena, and hematemesis. Patients should be apprised of the importance of this follow-up (see WARNINGS: Gastrointestinal Effects: Risk of Ulceration, Bleeding and Perforation).
- Piroxicam Capsules USP, like other NSAIDs, can cause serious skin side effects such as exfoliative dermatitis, SJS and TEN, which may result in hospitalizations and even death. Although serious skin reactions may occur without warning, patients should be alert for the signs and symptoms of skin rash and blisters, fever, or other signs hypersensitivity such as itching, and should ask for medical advice when observing any indicative signs or symptoms. Patients should be advised to stop the drug immediately if they develop any type of rash and contact their physicians as soon as possible.
- Patients should promptly report signs or symptoms of unexplained weight gain, or edema to their physicians.
- Patients should be informed of the warning signs and symptoms of hepatotoxicity (e.g., nausea, fatigue, lethargy, pruritus, jaundice, right upper quadrant tenderness and "flu-like" symptoms). If these occur, patients should be instructed to stop therapy and seek immediate medical therapy.
- Patients should be informed of the signs of an anaphylactoid reaction (e.g. difficulty breathing, swelling of the face or throat). If these occur, patients should be instructed to seek immediate emergency help (see WARNINGS).
- In late pregnancy, as with other NSAIDs, Piroxicam Capsules USP should be avoided because it may cause premature closure of the ductus arteriosus.

Laboratory Tests

Because serious GI tract ulcerations and bleeding can occur without warning symptoms, physicians should monitor for signs of symptoms of GI bleeding. Patients on long-term treatment with NSAIDs should have their CBC and a chemistry profile checked periodically. If clinical signs and symptoms consistent with liver or renal disease develop, systemic manifestations occur (e.g., eosinophilia, rash, etc.) or if abnormal liver tests persist or worsen, Piroxicam Capsules USP should be discontinued.

Drug InteractionsHighly Protein Bound Drugs

Piroxicam is highly protein bound and, therefore, might be expected to displace other protein bound drugs. Physicians should closely monitor patients for a change in dosage requirements when administering Piroxicam Capsules USP to patients on other highly protein bound drugs.

Aspirin

When piroxicam is administered with aspirin, its protein binding is reduced, although the clearance of free piroxicam is not altered. Plasma levels of piroxicam are depressed to approximately 80% of their normal values when piroxicam is administered (20 mg/day) in conjunction with aspirin (3900 mg/day). The clinical significance of this interaction is not known; however, as with other NSAIDs, concomitant administration of piroxicam and aspirin is not generally recommended because of the potential for increased adverse effects.

Methotrexate

NSAIDs have been reported to competitively inhibit methotrexate accumulation in rabbit kidney slices. This may indicate that they could enhance the toxicity of methotrexate. Caution should be used when NSAIDs are administered concomitantly with methotrexate.

ACE-Inhibitors

Reports suggest that NSAIDs may diminish the antihypertensive effect of ACE-inhibitors. This interaction should be given consideration in patients taking NSAIDs concomitantly with ACE-inhibitors.

Diuretics

Clinical studies, as well as postmarketing observations, have shown that Piroxicam Capsules USP can reduce the natriuretic effect of furosemide and thiazides in some patients. This response has been attributed to inhibition of renal prostaglandin synthesis. During concomitant therapy with NSAIDs, the patient should be observed closely for signs of renal failure (see WARNINGS: Renal Effects), as well as to assure diuretic efficacy.

Lithium

NSAIDs have produced an elevation of plasma lithium levels and a reduction in renal lithium clearance. The mean minimum lithium concentration increased 15% and the renal clearance was decreased by approximately 20%. These effects have been attributed to inhibition of renal prostaglandin synthesis by the NSAID. Thus, when NSAIDs and lithium are administered concurrently, subjects should be observed carefully for signs of lithium toxicity.

Warfarin

The effects of warfarin and NSAIDs on GI bleeding are synergistic, such that users of both drugs together have a risk of serious GI bleeding higher than users of either drug alone.

Carcinogenesis, Mutagenesis, Impairment of Fertility

Subacute, acute and chronic toxicity studies have been carried out in rats, mice, dogs and monkeys. The pathology most often seen was that characteristically associated with the animal toxicology of anti-inflammatory agents: renal papillary necrosis (see PRECAUTIONS) and gastrointestinal lesions.

Reproductive studies revealed no impairment of fertility in animals.

PregnancyTeratogenic EffectsPregnancy Category C

Reproductive studies conducted in rats and rabbits have not demonstrated evidence of developmental abnormalities. However, animal reproduction studies are not always predictive of human response. There are no adequate and well-controlled studies in pregnant women. Piroxicam Capsules USP is not recommended for use in pregnant women since safety has not been established in humans. Piroxicam Capsules USP should be used in pregnancy only if the potential benefit justifies the potential risk to the fetus.

Nonteratogenic Effects

Because of the known effects of nonsteroidal anti-inflammatory drugs on the fetal cardiovascular system (closure of ductus arteriosus), use during pregnancy (particularly late pregnancy) should be avoided. In animal studies of piroxicam, gastrointestinal tract toxicity was increased in pregnant females in the last trimester of pregnancy compared to nonpregnant females or females in earlier trimesters of pregnancy.

Labor and Delivery

In rat studies with NSAIDs, as with other drugs known to inhibit prostaglandin synthesis, an increased incidence of dystocia, delayed parturition, and decreased pup survival occurred. The effects of piroxicam on labor and delivery in pregnant women are unknown.

Nursing Mothers

Piroxicam is excreted into human milk. The presence in breast milk has been determined during initial and long-term conditions (52 days). Piroxicam appeared in breast milk at about 1% to 3% of the maternal concentration. No accumulation of piroxicam occurred in milk relative to that in plasma during treatment. Piroxicam Capsules USP is not recommended for use in nursing mothers.

Pediatric Use

Safety and effectiveness in pediatric patients have not been established.

Geriatric Use

As with any NSAID, caution should be exercised in treating the elderly (65 years and older). Most spontaneous reports of fatal GI events with NSAIDs are in the elderly or debilitated patients and, therefore, care should be taken in treating this population. In addition to a past history of ulcer disease, older age and poor general health status (among other factors) may increase the risk for GI bleeding. To minimize the potential risk of an adverse GI event, the lowest effective dose should be used for the shortest possible duration (see WARNINGS: Gastrointestinal (GI) Effects – Risk of GI Ulceration, Bleeding and Perforation).

As with all other NSAIDs, there is a risk of developing renal toxicity in patients in which renal prostaglandins have a compensatory role in maintenance of renal perfusion. Discontinuation of nonsteroidal anti-inflammatory drug therapy is usually followed by recovery to the pretreatment state (see Warnings: Renal Effects).

In general, dose selection for an elderly patient should be cautious, usually starting at the low end of the dosing range, reflecting a greater frequency of impaired drug elimination and of concomitant disease or other drug therapy.

ADVERSE REACTIONS SECTION

In patients taking Piroxicam Capsules USP or other NSAIDs, the most frequently reported adverse experiences occurring in approximately 1–10% of patients are:

Cardiovascular System: Edema. Digestive System: Anorexia, abdominal pain, constipation, diarrhea, dyspepsia, elevated liver enzymes, flatulence, gross bleeding/perforation, heartburn, nausea, ulcers (gastric/duodenal), vomiting. Hemic and Lymphatic System: Anemia, increased bleeding time. Nervous System: Dizziness, headache. Skin and Appendages: Pruritus, rash. Special Senses: Tinnitus. Urogenital System: Abnormal renal function.

Additional adverse experiences reported occasionally include:

Body As a Whole: Fever, infection, sepsis. Cardiovascular System: Congestive heart failure, hypertension, tachycardia, syncope. Digestive System: Dry mouth, esophagitis, gastritis, glossitis, hematemesis, hepatitis, jaundice, melena, rectal bleeding, stomatitis. Hemic and Lymphatic System: Ecchymosis, eosinophilia, epistaxis, leukopenia, purpura, petechial rash, thrombocytopenia. Metabolic and Nutritional: Weight changes. Nervous System: Anxiety, asthenia, confusion, depression, dream abnormalities, drowsiness, insomnia, malaise, nervousness, paresthesia, somnolence, tremors, vertigo. Respiratory System: Asthma, dyspnea. Skin and Appendages: Alopecia, bruising, desquamation, erythema, photosensitivity, sweat. Special Senses: Blurred vision. Urogenital System: Cystitis, dysuria, hematuria, hyperkalemia, interstitial nephritis, nephrotic syndrome, oliguria/polyuria, proteinuria, renal failure.

Other adverse reactions which occur rarely are:

Body As a Whole: Anaphylactic reactions, appetite changes, death, flu-like syndrome, pain (colic), serum sickness. Cardiovascular System: Arrhythmia, exacerbation of angina, hypotension, myocardial infarction, palpitations, vasculitis. Digestive System: Eructation, liver failure, pancreatitis. Hemic and Lymphatic System: Agranulocytosis, hemolytic anemia, aplastic anemia, lymphadenopathy, pancytopenia. Hypersensitivity: Positive ANA. Metabolic and Nutritional: Hyperglycemia, hypoglycemia. Nervous System: Akathisia, convulsions, coma, hallucinations, meningitis, mood alterations. Respiratory: Respiratory depression, pneumonia. Skin and Appendages: Angioedema, toxic epidermal necrosis, erythema multiforme, exfoliative dermatitis, onycholysis, Stevens-Johnson syndrome, urticaria, vesiculobullous reaction. Special Senses: Conjunctivitis, hearing impairment, swollen eyes.

OVERDOSAGE SECTION

Symptoms following acute NSAID overdoses are usually limited to lethargy, drowsiness, nausea, vomiting, and epigastric pain, which are generally reversible with supportive care. Gastrointestinal bleeding can occur. Hypertension, acute renal failure, respiratory depression and coma may occur, but are rare. Anaphylactoid reactions have been reported with therapeutic ingestion of NSAIDs, and may occur following an overdose.

Patients should be managed by symptomatic and supportive care following an NSAID overdose. There are no specific antidotes. Emesis and/or activated charcoal (60–100 g in adults, 1–2 g/kg in children) and/or osmotic cathartic may be indicated. The long plasma half-life of piroxicam should be considered when treating an overdose with piroxicam. Experiments in dogs have demonstrated that the use of multiple-dose treatments with activated charcoal could reduce the half-life of piroxicam by more than 50% and systemic bioavailability by as much as 37% when activated charcoal is given as late as 6 hours after ingestion of piroxicam. Forced diuresis, alkalinization of urine, hemodialysis, or hemoperfusion may not be useful due to high protein binding.

DOSAGE & ADMINISTRATION SECTION

Carefully consider the potential benefits and risks of Piroxicam Capsules USP and other treatment options before deciding to use Piroxicam Capsules USP. Use the lowest effective dose for the shortest duration consistent with individual patient treatment goals (see WARNINGS).

After observing the response to initial therapy with Piroxicam Capsules USP, the dose and frequency should be adjusted to suit an individual patient's needs.

For the relief of rheumatoid arthritis and osteoarthritis, the recommended dose is 20 mg given orally once per day. If desired, the daily dose may be divided. Because of the long half-life of Piroxicam Capsules USP, steady-state blood levels are not reached for 7–12 days. Therefore, although the therapeutic effects of piroxicam are evident early in treatment, there is a progressive increase in response over several weeks and the effect of therapy should not be assessed for two weeks.

HOW SUPPLIED SECTION

Piroxicam Capsules USP for oral administration:

Bottles of 100's: 10 mg Capsule, (NDC#29033-012-01) Swedish Orange Opaque cap is imprinted with "NP" above "10" in black with a lvory opaque body.

Bottles of 100's: 20 mg Capsule, (NDC#29033-013-01) Swedish Orange Opaque cap is imprinted with "NP" above "20" in black with a Swedish Orange Opaque body.

Bottles of 500's: 20 mg Capsule, (NDC#29033-013-05) Swedish Orange Opaque Cap is imprinted with "NP" above "20" in black with a Swedish Orange Opaque body.

Store at 20°-25°C (68°-77°F); excursions permitted to 15°-30°C (59°-86°F) [see USP Controlled Room Temperature]

Dispense in a tight,light-resistant container as defined in the USP.